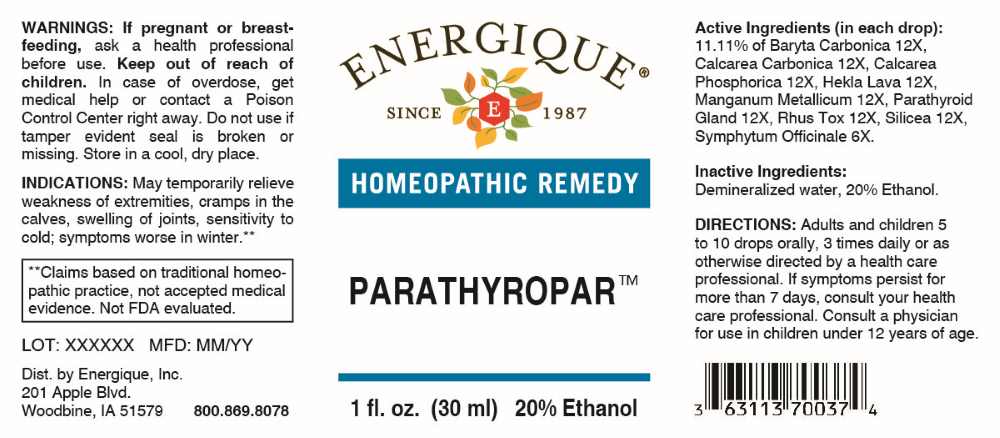 DRUG LABEL: Parathyropar
NDC: 44911-0902 | Form: LIQUID
Manufacturer: Energique, Inc.
Category: homeopathic | Type: HUMAN OTC DRUG LABEL
Date: 20260105

ACTIVE INGREDIENTS: COMFREY ROOT 6 [hp_X]/1 mL; BARIUM CARBONATE 12 [hp_X]/1 mL; OYSTER SHELL CALCIUM CARBONATE, CRUDE 12 [hp_X]/1 mL; TRIBASIC CALCIUM PHOSPHATE 12 [hp_X]/1 mL; HEKLA LAVA 12 [hp_X]/1 mL; MANGANESE 12 [hp_X]/1 mL; BOS TAURUS PARATHYROID GLAND 12 [hp_X]/1 mL; TOXICODENDRON PUBESCENS LEAF 12 [hp_X]/1 mL; SILICON DIOXIDE 12 [hp_X]/1 mL
INACTIVE INGREDIENTS: WATER; ALCOHOL

DRUG FACTS:

ACTIVE INGREDIENTS:

(in each drop): 11.11% of Baryta Carbonica 12X, Calcarea Carbonica 12X, Calcarea Phosphorica12X, Hekla Lava 12X, Manganum Metallicum 12X, Parathyroid Gland 12X, Rhus Tox 12X, Silicea 12X, Symphytum Officinale 6X.

PURPOSE:

May temporarily relieve weakness of extremities, cramps in the calves, swelling of joints, sensitivity to cold; symptoms worse in winter.**

**Claims based on traditional homeopathic practice, not accepted medical evidence. Not FDA evaluated.

WARNINGS:

If pregnant or breast-feeding, ask a health professional before use.

Keep out of reach of children. In case of overdose, get medical help or contact a Poison Control Center right away.

Do not use if tamper evident seal is broken or missing.

Store in a cool, dry place.

KEEP OUT OF REACH OF CHILDREN:

In case of overdose, get medical help or contact a Poison Control Center right away.

DIRECTIONS:

Adults and children 5 to 10 drops orally, 3 times daily or as otherwise directed by a health care professional. If symptoms persist for more than 7 days, consult your health care professional. Consult a physician for use in children under 12 years of age.

INDICATIONS:

May temporarily relieve weakness of extremities, cramps in the calves, swelling of joints, sensitivity to cold; symptoms worse in winter.**

**Claims based on traditional homeopathic practice, not accepted medical evidence. Not FDA evaluated.

INACTIVE INGREDIENTS:

Demineralized water, 20% Ethanol.

QUESTIONS:

Dist. by Energique, Inc.
201 Apple Blvd.
Woodbine, IA 51579

800.869.8078

PACKAGE LABEL DISPLAY:

ENERGIQUE
SINCE 1987
HOMEOPATHIC REMEDY
PARATHYROPAR
1 fl. oz. (30 ml)